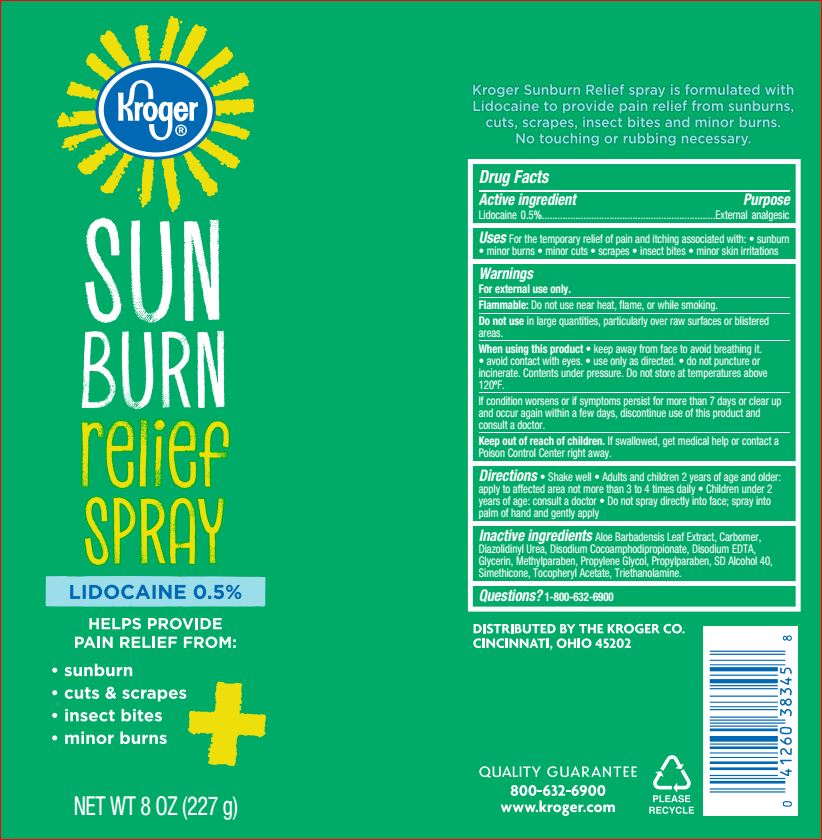 DRUG LABEL: Sunburn Relief
NDC: 59450-778 | Form: spray
Manufacturer: Kroger
Category: otc | Type: HUMAN OTC DRUG LABEL
Date: 20180720

ACTIVE INGREDIENTS: Lidocaine 0.5 g/100 g
INACTIVE INGREDIENTS: ALOE VERA LEAF; Diazolidinyl Urea; Disodium Cocoamphodipropionate; EDETATE DISODIUM; Glycerin; Methylparaben; Propylene Glycol; Propylparaben; ALCOHOL; .ALPHA.-TOCOPHEROL ACETATE; TROLAMINE

Drug Facts

Active ingredient Purpose

Lidocaine 0.5% External analgesic

Uses

Temporarily relieves pain and itching due to

• sunburn • minor burns • minor cuts • scrapes

• insect bites • minor skin irritation

Warnings

For external use only

When using this product

- keep out of your eyes
- use only as directed
- do not puncture or incinerate. Contents under pressure. Do not store at temperature above 120F.

Keep out of reach of the children

If swallowed, get medical help or contact a Poison Control Center right away

Directions

• shake well
• adults and children 2 years of age and older: apply to affected area, not more than 3 to 4 times daily
• children under 2 years of age: ask a doctor

• to apply to face, spray into palm of hand and gently apply

Inactive ingredients

Aloe Barbadensis Leaf Juice, Carbomer, Diazolidinyl Urea, Disodium Cocoamphodipropionate, Disodium EDTA, Glycerin, Methylparaben, Propylene Glycol, Propylparaben, SD Alcohol 40, Simethicone, Tocopheryl Acetate, Triethanolamine